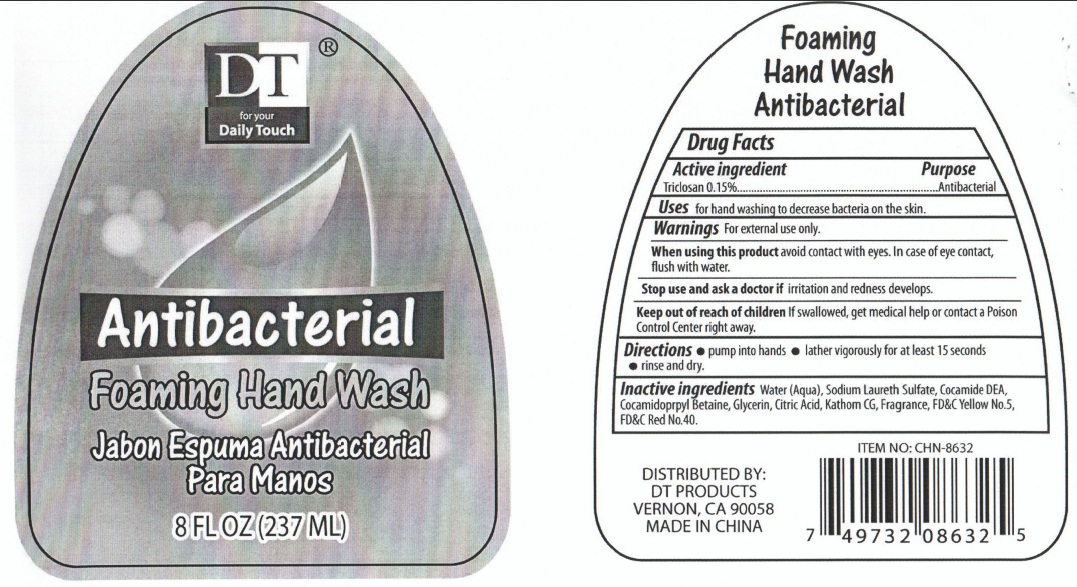 DRUG LABEL: DT Antibacterial Foaming Hand Wash
NDC: 50523-632 | Form: LIQUID
Manufacturer: Volume Distributors, Inc.
Category: otc | Type: HUMAN OTC DRUG LABEL
Date: 20101222

ACTIVE INGREDIENTS: TRICLOSAN 0.15 mL/100 mL
INACTIVE INGREDIENTS: WATER; SODIUM LAURETH SULFATE; COCO DIETHANOLAMIDE; COCAMIDOPROPYL BETAINE; GLYCERIN; CITRIC ACID MONOHYDRATE; FD&C YELLOW NO. 5

DT Antibacterial Foaming Hand Wash

Active Ingredient

Triclosan 0.15%

Purpose

Antibacterial

Uses:

for hand washing to decrease bacteria on the skin.

Warnings for external use only.

When using this product avoid contact with eyes. In case of eye contact, flush with water.

Stop use and ask a doctor if irritation and redness develops.

Keep out of reach of children. If swallowed, get medical help or contact a Poison Control Center right away.

Directions

pump into hands

lather vigorously for at least 15 seconds

rinse and dry thoroughly.

Inactive Ingredients

Water (aqua), sodium laureth sulfate, cocamide DEA, cocamidopropyl betaine, glycerin, citric acid, kathom CG, Fragrance, FD and C yellow No.5, FDandC Red No 40.

PACKAGE LABEL

DT for your Daily Touch
Antibacterial
foaming Hand Wash
Distributed by DT Products
Vernon, CA 90058
MADE IN CHINA